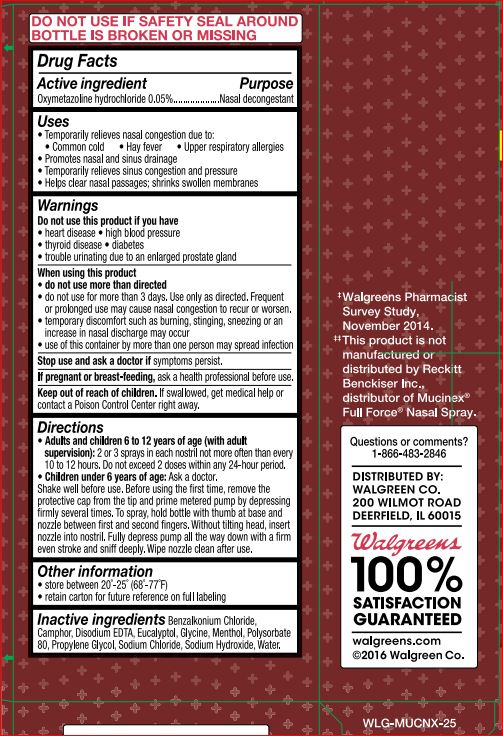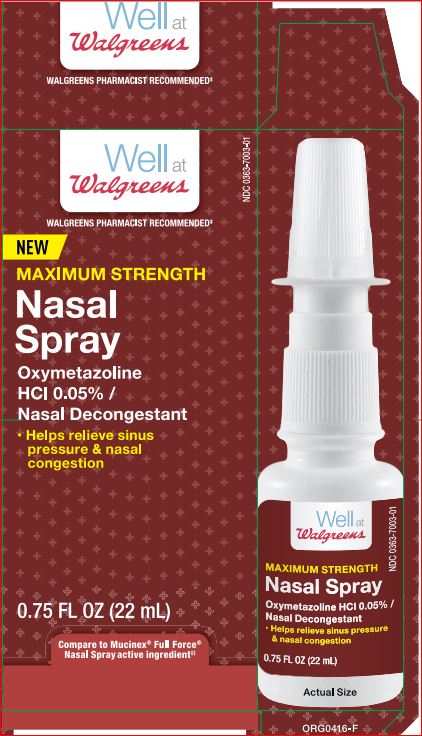 DRUG LABEL: Maximum Strenth Nasal
NDC: 0363-7003 | Form: LIQUID
Manufacturer: Walgreens
Category: otc | Type: HUMAN OTC DRUG LABEL
Date: 20180219

ACTIVE INGREDIENTS: Oxymetazoline Hydrochloride 0.05 g/100 mL
INACTIVE INGREDIENTS: Benzalkonium Chloride; CAMPHOR (SYNTHETIC); EDETATE DISODIUM; Eucalyptol; Glycine; Menthol; Polysorbate 80; Propylene Glycol; Sodium Chloride; Sodium Hydroxide; water

Walgreens
Drug Facts

Active ingredient Purpose

Oxymetazoline Hydrochloride - 0.05% Nazal Decongestant

Uses

For the temporary relief of nasal congestion due to the common cold, hay fever or other upper respiratory allergies.

Warnings

Do not use this product if person has heart disease, high blood pressure, thyroid disease, diabetes, or if adult has difficulty in urination due to enlargement of the prostate gland unless directed by a doctor.

When using this product

Do not exceed recommended dosage

Do not use this product for more than 3 days. Use only as directed. Frequent or prolonged use may cause nasal congestion to recur or worsen. If symptoms persist, consult a doctor.This product may cause temporary discomfort such as burning, stinging, sneezing, or an increase in nasal discharge. The use of this container by more than one person may spread infection.

Directions

Adults and children 6 to under 12 years of age (with adult supervision): 2 or 3 sprays in each nostril not more often than every 10 to 12 hours. Do not exceed 2 doses in any 24-hour period. Children under 6 years of age: consult a doctor.

Inactive ingredients

Benzalkonium Chloride
Camphor
Disodium EDTA
Eucalyptol
Glycine
Menthol
Polysorbate 80
Propylene Glycol
Sodium Chloride
Sodium Hydroxide
Water